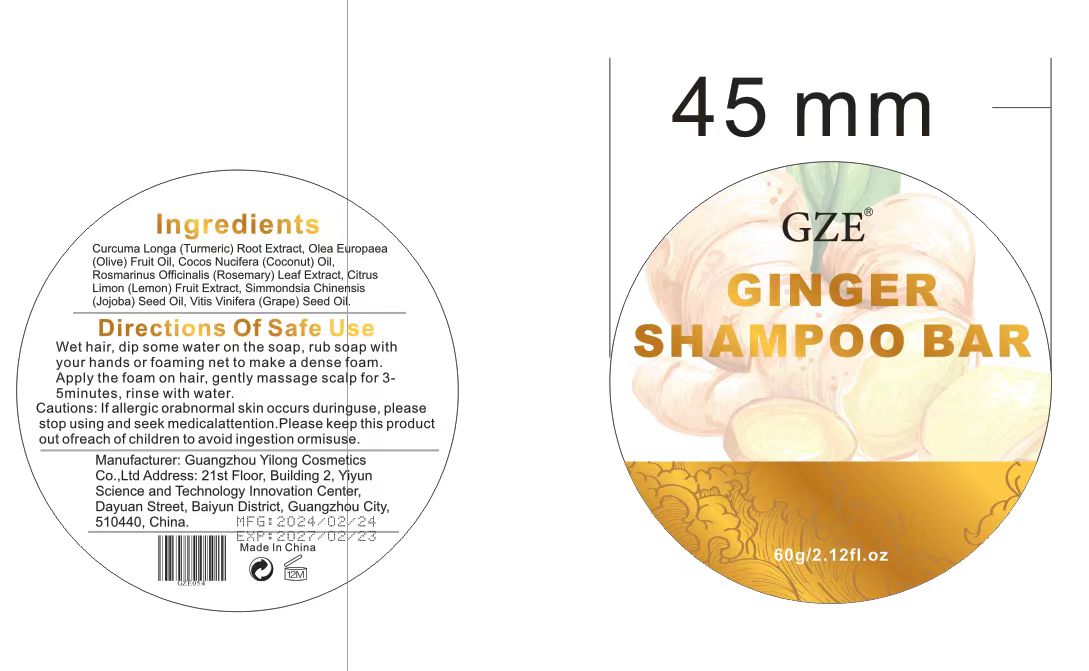 DRUG LABEL: GZE Ginger ShampooBar
NDC: 74458-054 | Form: SOAP
Manufacturer: Guangzhou Yilong Cosmetics Co., Ltd
Category: otc | Type: HUMAN OTC DRUG LABEL
Date: 20241024

ACTIVE INGREDIENTS: ROSMARINUS OFFICINALIS (ROSEMARY) LEAF EXTRACT 15 g/100 g
INACTIVE INGREDIENTS: VITIS VINIFERA (GRAPE) SEED OIL; SIMMONDSIA CHINENSIS (JOJOBA) SEED OIL; CURCUMA LONGA (TURMERIC) ROOT EXTRACT; OLEA EUROPAEA (OLIVE) FRUIT OIL; CITRUS LIMON (LEMON) FRUIT EXTRACT; COCOS NUCIFERA (COCONUT) OIL

GZE GINGER SHAMPOO BAR

ACTIVE INGREDIENT

Rosmarinus Officinalis (Rosemary) Leaf Extract 15%

INACTIVE INGREDIENT

Curcuma Longa (Turmeric) Root Extract

Olea Europaea (Olive) Fruit Oil

Cocos Nucifera (Coconut) Oil

Citrus Limon (Lemon) Fruit Extract

Simmondsia Chinensis (Jojoba) Seed Oil

Vitis Vinifera (Grape) Seed Oil

INDICATIONS AND USAGE

Wet hair, dip some water on the soap, rub soap with your hands or foaming net to make a dense foam.Apply the foam on hair, gently massage scalp for 35 minutes,rinse with water.

PURPOSE

Anti-dandruff.

WARNINGS

For external use only.

Stop use and ask a doctor if rash occurs.

Do not use on damaged or broken skin.

When using this product keep out of eyes. Rinse with water to remove.

Keep out of reach of children. If swallowed, get medical help or contact a Poison Control Center right away.

DOSAGE AND ADMINISTRATION

Wet hair, dip some water on the soap, rub soap with your hands or foaming net to make a dense foam.Apply the foam on hair, gently massage scalp for 35 minutes,rinse with water.